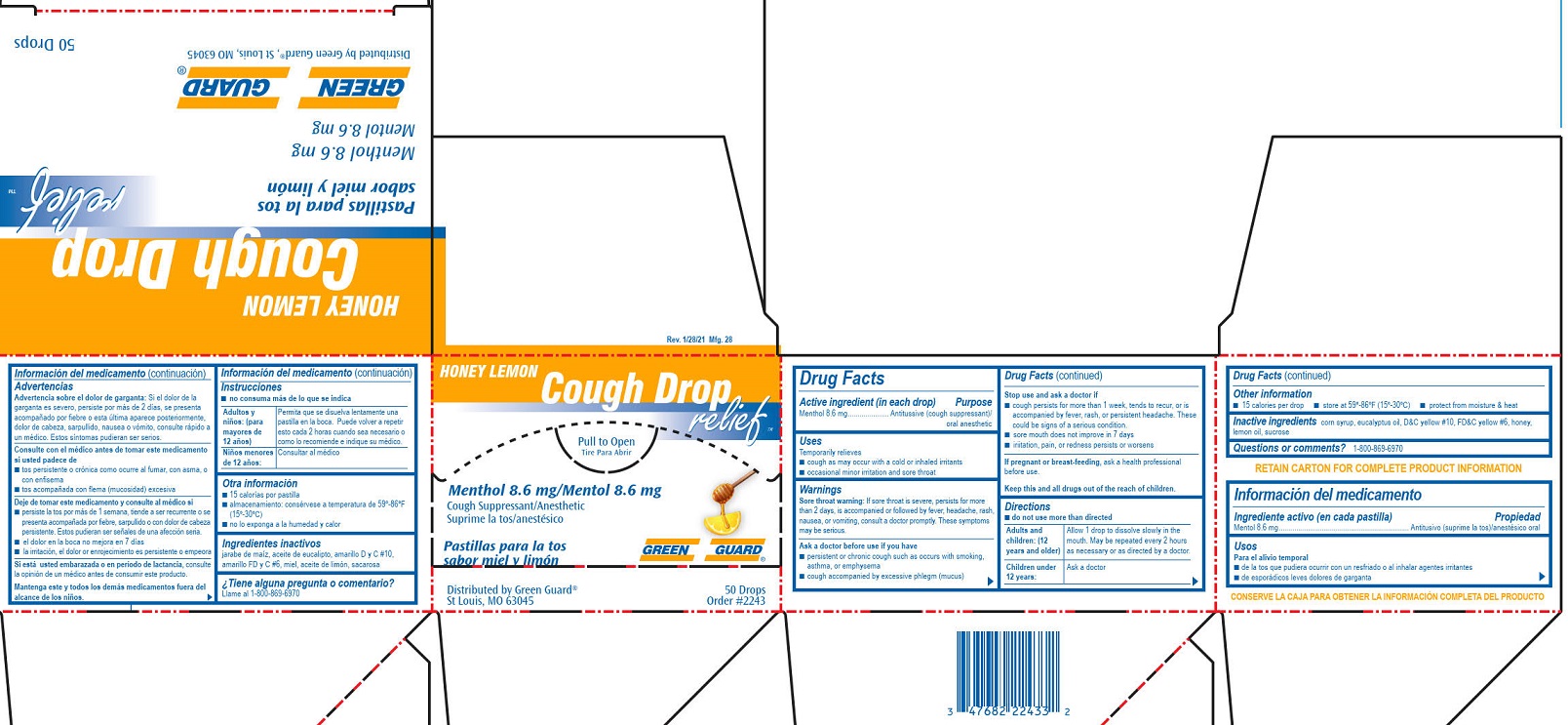 DRUG LABEL: Green Guard Honey Lemon Cough Drop
NDC: 47682-040 | Form: LOZENGE
Manufacturer: Unifirst First Aid Corporation
Category: otc | Type: HUMAN OTC DRUG LABEL
Date: 20250908

ACTIVE INGREDIENTS: MENTHOL 8.6 mg/1 1
INACTIVE INGREDIENTS: FD&C YELLOW NO. 6; EUCALYPTUS OIL; HONEY; LEMON OIL; SUCROSE; D&C YELLOW NO. 10; CORN SYRUP

Green Guard Honey Lemon Cough Drop

Drug Facts

Active ingredient (in each drop)

Menthol 8.6 mg

Purpose

Antitussive (cough suppressant)/oral anesthetic

Uses

Temporarily relieves

■ cough as may occur with a cold or inhaled irritants

■ occasional minor irritation and sore throat

Warnings

Sore throat warning: If sore throat is severe, persists for more than 2 days, is accompanied or followed by fever, headache, rash, nausea, or vomiting, consult a doctor promptly. These symptoms may be serious.

Ask a doctor before use if you have

■ persistent or chronic cough such as occurs with smoking, asthma, or emphysema

■ cough accompanied by excessive phlegm (mucus)

Stop use and ask a doctor if

■ cough persists for more than 1 week, tends to recur, or is accompanied by fever, rash, or persistent
headache. These could be signs of a serious condition.

■ sore mouth does not improve in 7 days

■ irritation, pain, or redness persists or worsens

PREGNANCY OR BREAST FEEDING

If pregnant or breast-feeding, ask a health professional before use.

KEEP OUT OF REACH OF CHILDREN

Keep this and all drugs out of the reach of children.

Directions

■ do not use more than directed

Adults and children: (12 years and older)

Allow 1 drop to dissolve slowly in the mouth. May be repeated every 2 hours as necessary or as directed by a doctor.

Children under 12 years:

Ask a doctor

Other information

■ 15 calories per drop

■ store at 59º-86ºF (15º-30ºC)

■ protect from moisture & heat

INACTIVE INGREDIENT

Inactive ingredients corn syrup, eucalyptus oil, D&C yellow #10, FD&C yellow #6, honey, lemon oil, sucrose

Questions or comments? 1-800-869-6970

Green Guard Honey Lemon Cough Drop Label

Green Guard®

Honey Lemon

Cough Drop relief™

Pull to Open

Tire Para Abrir

Menthol 8.6mg/Mentol 8.6mg

Cough Supressant/ Anesthetic

Suprime la tos/ anestesico

Pastillas par la tos

sabor miel y limon

Distributed by Green Guard®, St. Louis, MO 63045

50 Drops

Order #2243